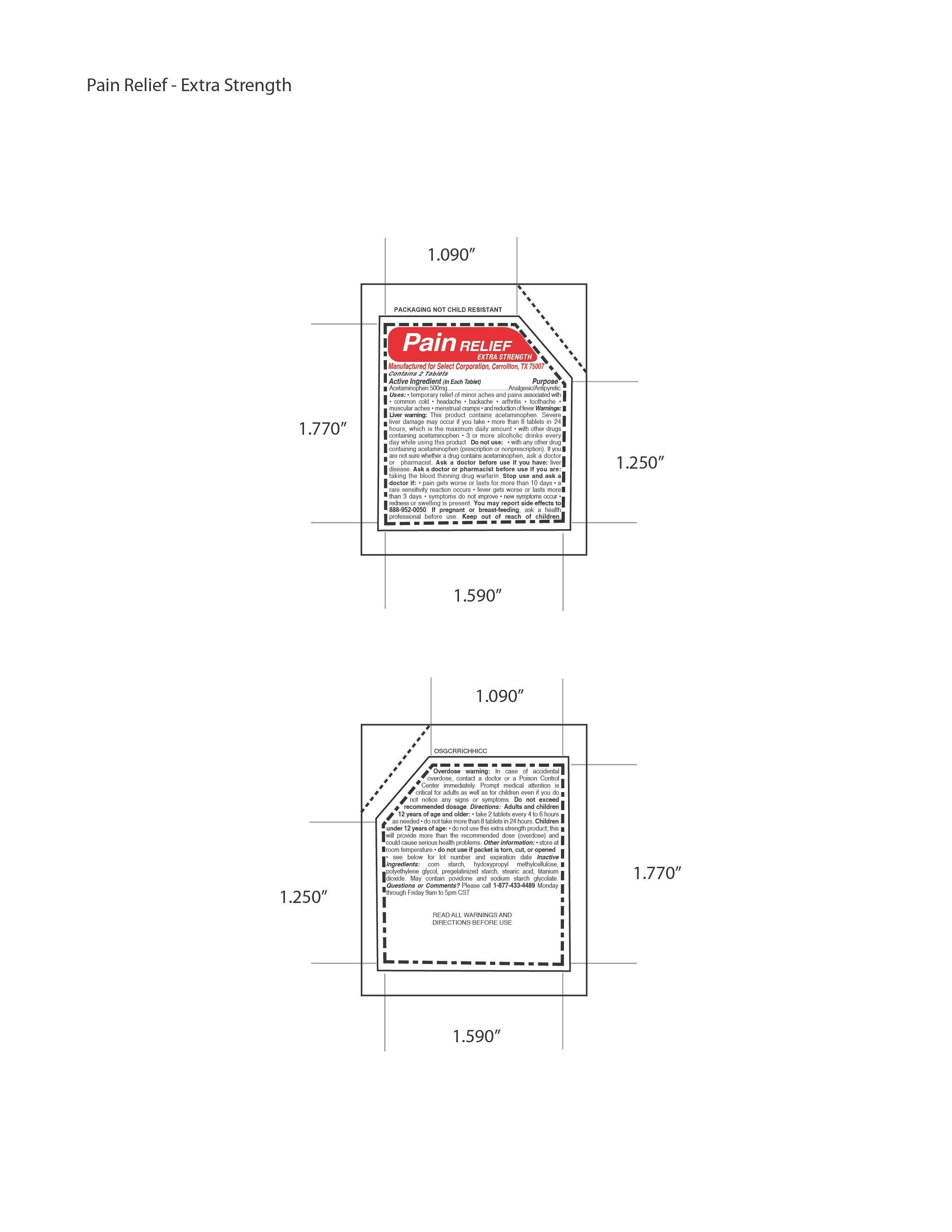 DRUG LABEL: Pain Relief Extra Strength
NDC: 52904-446 | Form: TABLET
Manufacturer: Select Corporation
Category: otc | Type: HUMAN OTC DRUG LABEL
Date: 20121015

ACTIVE INGREDIENTS: ACETAMINOPHEN 500 mg/1 1
INACTIVE INGREDIENTS: STARCH, CORN; POLYETHYLENE GLYCOL 300; STEARIC ACID; TITANIUM DIOXIDE; SODIUM STARCH GLYCOLATE TYPE A POTATO; POVIDONE K29/32

Drug Facts

Active Ingredients

Acetaminophen 500mg

PURPOSE

Analgesic, Antipyretic

DOSAGE AND ADMINISTRATION

Directions: Adults and children
12 years of age and older: • take 2 tablets every 4 to 6 hours
as needed • do not take more than 8 tablets in 24 hours. Children
under 12 years of age: • do not use this extra strength product; this
will provide more than the recommended dose (overdose) and
could cause serious health problems.

INDICATIONS AND USAGE

Uses: • temporary relief of minor aches and pains associated with
• common cold • headache • backache • arthritis • toothache •
muscular aches • menstrual cramps • and reduction of fever

Warnings:
Liver warning: This product contains acetaminophen. Severe
liver damage may occur if you take • more than 8 tablets in 24
hours, which is the maximum daily amount • with other drugs
containing acetaminophen • 3 or more alcoholic drinks every
day while using this product Do not use: • with any other drug
containing acetaminophen (prescription or nonprescription). If you
are not sure whether a drug contains acetaminophen, ask a doctor
or pharmacist. Ask a doctor before use if you have: liver
disease. Ask a doctor or pharmacist before use if you are:
taking the blood thinning drug warfarin. Stop use and ask a
doctor if: • pain gets worse or lasts for more than 10 days • a
rare sensitivity reaction occurs • fever gets worse or lasts more
than 3 days • symptoms do not improve • new symptoms occur •
redness or swelling is present. You may report side effects to
888-952-0050.

If pregnant or breast-feeding, ask a health
professional before use.

KEEP OUT OF REACH OF CHILDREN.

Inactive ingredients: corn starch, hydoxypropyl methylcellulose,
polyethylene glycol, pregelatinized starch, stearic acid, titanium
dioxide. May contain povidone and sodium starch glycolate

PACKAGE LABEL

MM1